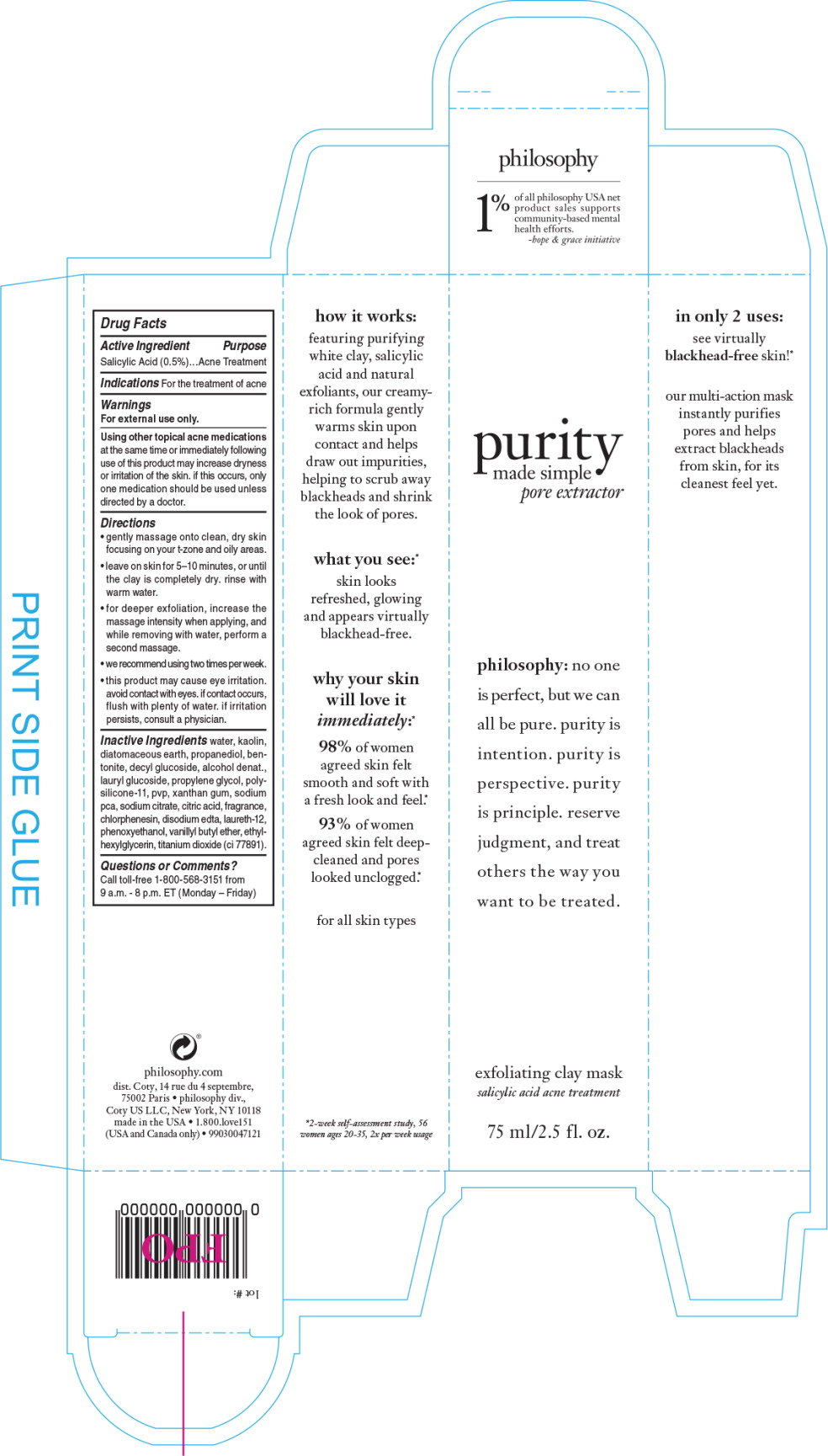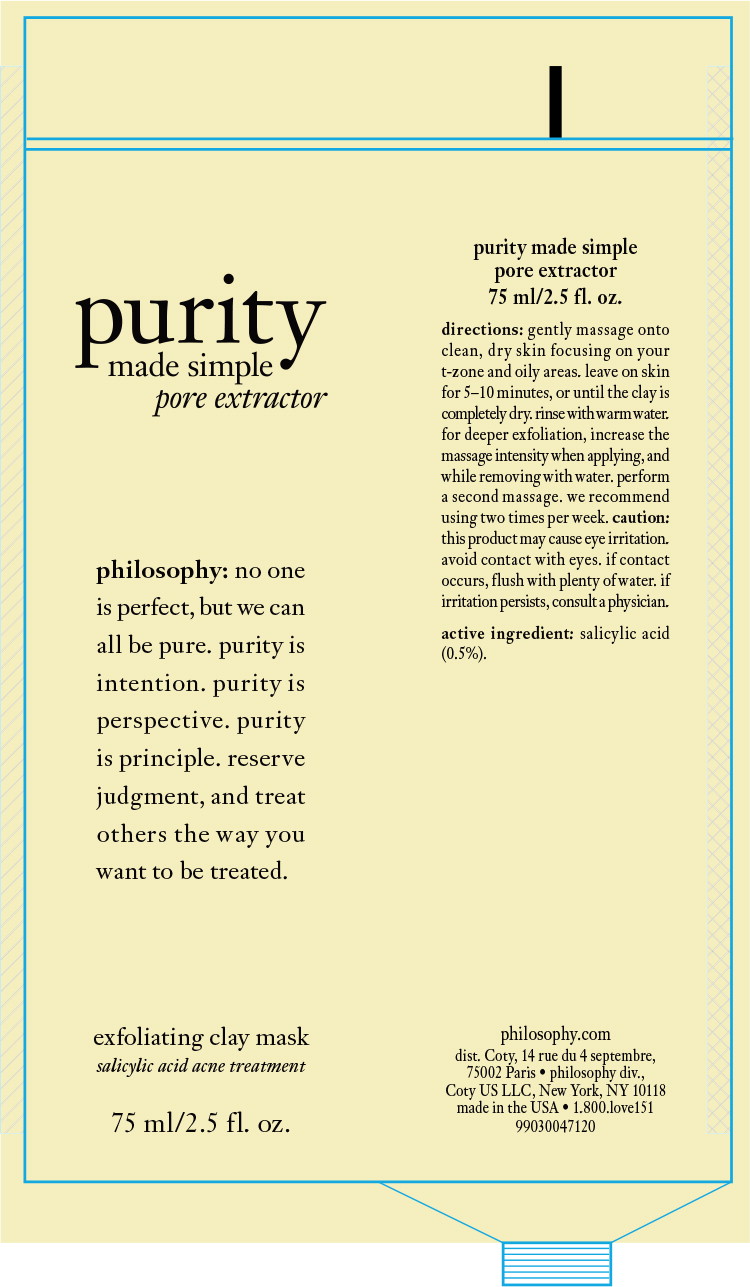 DRUG LABEL: purity made simple
NDC: 50184-1060 | Form: CREAM
Manufacturer: Philosophy, Inc.
Category: otc | Type: HUMAN OTC DRUG LABEL
Date: 20241119

ACTIVE INGREDIENTS: SALICYLIC ACID 0.5 ug/1 mL
INACTIVE INGREDIENTS: WATER; KAOLIN; DIATOMACEOUS EARTH; PROPANEDIOL; BENTONITE; DECYL GLUCOSIDE; ALCOHOL; LAURYL GLUCOSIDE; PROPYLENE GLYCOL; POVIDONE, UNSPECIFIED; XANTHAN GUM; SODIUM PYRROLIDONE CARBOXYLATE; SODIUM CITRATE; CITRIC ACID MONOHYDRATE; CHLORPHENESIN; EDETATE DISODIUM; LAURETH-12; PHENOXYETHANOL; VANILLYL BUTYL ETHER; ETHYLHEXYLGLYCERIN; TITANIUM DIOXIDE

Drug Facts

Active Ingredient

Salicylic Acid (0.5%)

Purpose

Acne Treatment

Indications

For the treatment of acne

Warnings

For external use only.

Using other topical acne medications at the same time or immediately following use of this product may increase dryness or irritation of the skin. if this occurs, only one medication should be used unless directed by a doctor.

Directions

KEEP OUT OF REACH OF CHILDREN

- gently massage onto clean, dry skin focusing on your t-zone and oily areas.
- leave on skin for 5–10 minutes, or until the clay is completely dry. rinse with warm water.
- for deeper exfoliation, increase the massage intensity when applying, and while removing with water, perform a second massage.
- we recommend using two times per week.
- this product may cause eye irritation. avoid contact with eyes. if contact occurs, flush with plenty of water. if irritation persists, consult a physician.

Inactive Ingredients

water, kaolin, diatomaceous earth, propanediol, bentonite, decyl glucoside, alcohol denat., lauryl glucoside, propylene glycol, polysilicone-11, pvp, xanthan gum, sodium pca, sodium citrate, citric acid, fragrance, chlorphenesin, disodium edta, laureth-12, phenoxyethanol, vanillyl butyl ether, ethylhexylglycerin, titanium dioxide (ci 77891).

Questions or Comments?

Call toll-free 1-800-568-3151 from 9 a.m. - 8 p.m. ET (Monday – Friday)

Principal Display Panel - 75 mL Carton Label

purity
made simple
pore extract

philosophy: no one
is perfect, but we can
all be pure. purity is
intention. purity is
perspective. purity
is principle. reserve
judgment, and treat
others the way you
want to be treated.

exfoliating clay mask
salicylic acid acne treatment

75 ml/2.5 fl. oz.

Principal Display Panel - 75 mL Tube Label

purity
made simple
pore extract

philosophy: no one
is perfect, but we can
all be pure. purity is
intention. purity is
perspective. purity
is principle. reserve
judgment, and treat
others the way you
want to be treated.

exfoliating clay mask
salicylic acid acne treatment

75 ml/2.5 fl. oz.